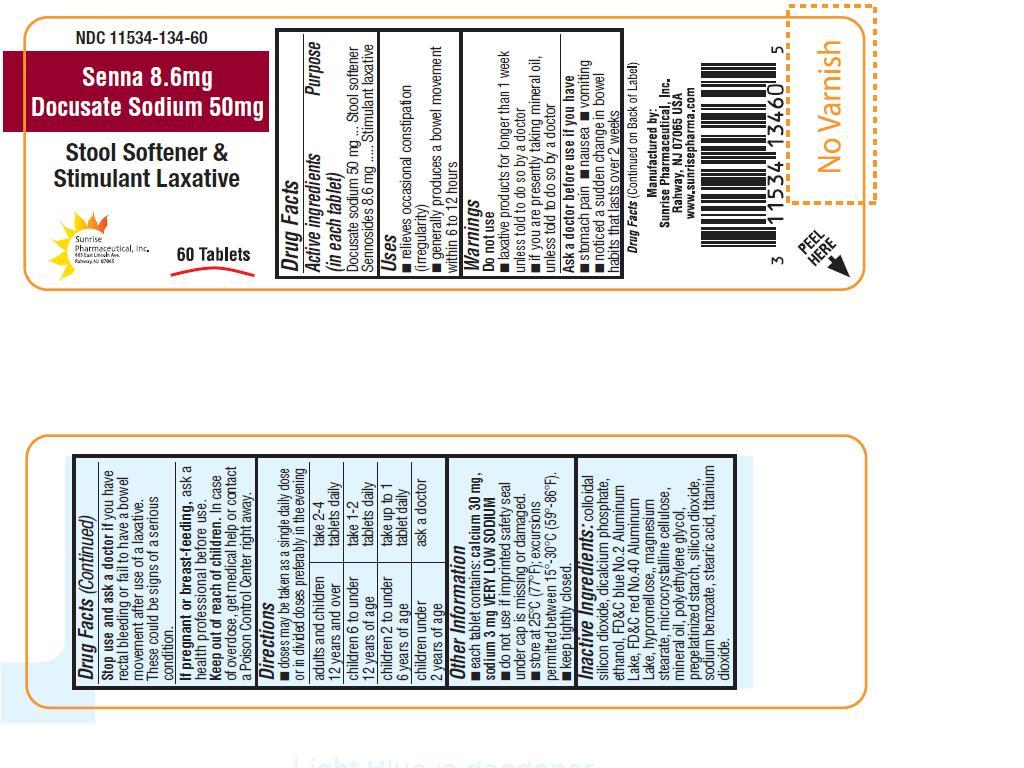 DRUG LABEL: Senna and Docusate Sodium
NDC: 11534-134 | Form: TABLET, FILM COATED
Manufacturer: Sunrise Pharmaceutical Inc
Category: otc | Type: HUMAN OTC DRUG LABEL
Date: 20130802

ACTIVE INGREDIENTS: DOCUSATE SODIUM 50 mg/1 1; SENNOSIDES 8.6 mg/1 1
INACTIVE INGREDIENTS: DIBASIC CALCIUM PHOSPHATE DIHYDRATE; SILICON DIOXIDE; ALCOHOL; FD&C BLUE NO. 2; FD&C RED NO. 40; HYPROMELLOSE 2208 (100 MPA.S); MAGNESIUM STEARATE; CELLULOSE, MICROCRYSTALLINE; MINERAL OIL; POLYETHYLENE GLYCOLS; STARCH, CORN; SODIUM BENZOATE; STEARIC ACID; TITANIUM DIOXIDE

Senna and Docusate Sodium Film Coated Red Tablets 8.6 mg/ 50 mg Laxative

OTC - ACTIVE INGREDIENT

Docusate sodium 50 mg, Sennoside 8.6 mg.

OTC - PURPOSE

Stimulant laxative.

INDICATIONS AND USAGE

For temporary relief of occasional constipation and irregularity.

This product generally produces bowel movement in 6 to 12 hours.

WARNINGS

Do not use:

laxative products for longer than 1 week unless told to do so by a doctor.

if you are presently taking mineral oil, unless told to do so by a doctor

OTC - ASK DOCTOR

Before use if you have:

Stomach pain, nausea or vomiting

Noticed a sudden change in bowel habits that lasts over 2 weeks.

OTC - STOP USE

If you have rectal bleeding or fail to have bowel movement after use of a laxative. This could be a serious condition.

OTC - PREGNANCY OR BREAST FEEDING

Ask a health professional before use.

OTC - KEEP OUT OF REACH OF CHILDREN

In case of overdose, get medical help or contact a Poison Control Center right away.

DOSAGE AND ADMINISTRATION

Drink with a full glass of water with each dose

Adults and children 12 years and over | take 2 - 4 tablets daily
Children 6 to under 12 years | take 1 - 2 tablets daily
Children 2 to under 6 years | take up to 1 tablet daily
Children under 2 years of age | Ask a doctor

OTHER INFORMATION

Each tablet contains: calcium 30 mg, sodium 3 mg VERY LOW SODIUM.

Do not use if the imprinted safety seal under cap is missing or damaged.

Store at at 25°C (77°F); excursions permitted between 15(-30(C (59(-86(F)

Keep tightly closed.

INACTIVE INGREDIENT

Colloidal silicon dioxide, dicalcium phosphate, ethanol, FD&C blue #2, FD&C red #40, hypromellose, magnesium stearate, microcrystalline cellulose, mineral oil, polyethylene glycol, pregelatinized starch, silicon dioxide, sodium benzoate, stearic acid, titanium dioxide.